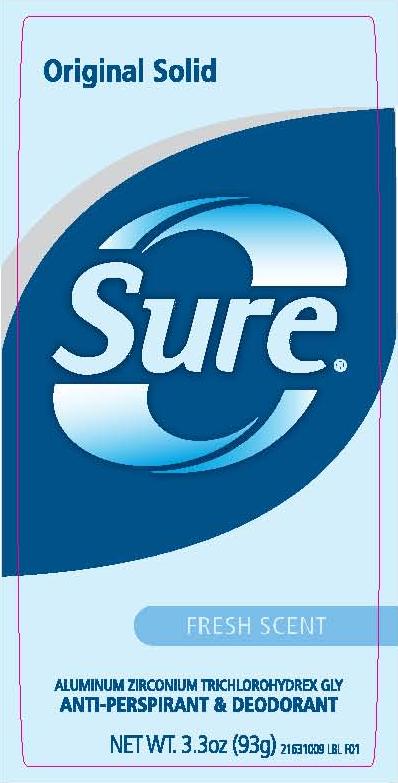 DRUG LABEL: Sure Original Solid Fresh Scent
NDC: 41595-5515 | Form: STICK
Manufacturer: Idelle Labs, Ltd
Category: otc | Type: HUMAN OTC DRUG LABEL
Date: 20120510

ACTIVE INGREDIENTS: ALUMINUM ZIRCONIUM TRICHLOROHYDREX GLY 16 g/100 g
INACTIVE INGREDIENTS: CYCLOMETHICONE 5; STEARYL ALCOHOL; TALC; DIMETHICONE; HYDROGENATED CASTOR OIL; LOW DENSITY POLYETHYLENE; SILICON DIOXIDE; PROPYLENE GLYCOL; DOCOSANOL

Sure Original Solid Antiperspirant Deodorant Fresh

Sure Original Solid Fresh Scent
Aluminum Zirconium Trichlorohydrex GLY
Anti-perspirant and Deodorant
MM1

Active Ingredient

Aluminum Zirconium Trichlorohydrex GLY 16% (anhydrous)

Purpose

Antiperspirant

Uses

Reduces underarm wetness

Warnings

For external use only.

Do not use on broken skin

Ask a doctor before use if you have kidney disease

Stop use

Stop use if rash or irritation occurs

Keep out of reach of children. If swallowed, get medical help or contact a Poison Control Center right away.

Directions

Apply to underarms only

Inactive Ingredients

Cyclopentasiloxane, Stearyl Alcohol, Talc, Dimethicone, Hydrogenated Castor Oil, Fragrance, Polyethylene, Silica, Dipropylene Glycol, Behenyl Alcohol

Questions

1-800-944-4477
www.suredeodorant.com
© Idelle Labs, Ltd. All rights reserved
Made in Canada and distributed by Idelle Labs, Ltd., El Paso, TX 79912
Sure® is a registered trademark of Helen of Troy Limited

label